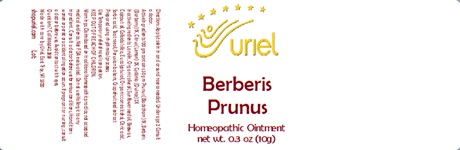 DRUG LABEL: Berberis Prunus
NDC: 48951-2148 | Form: OINTMENT
Manufacturer: Uriel Pharmacy Inc.
Category: homeopathic | Type: HUMAN OTC DRUG LABEL
Date: 20241205

ACTIVE INGREDIENTS: BERBERIS VULGARIS ROOT BARK 1 [hp_X]/1 g; LEMON 2 [hp_X]/1 g; QUINCE 2 [hp_X]/1 g; SLOE 1 [hp_X]/1 g
INACTIVE INGREDIENTS: LANOLIN; OLIVE OIL; YELLOW WAX; CAJUPUT OIL; TEA TREE OIL; EUCALYPTUS OIL; CITRIC ACID MONOHYDRATE; SORBIC ACID; BALSAM PERU; CITRUS PARADISI SEED; SUNFLOWER OIL; ALCOHOL

Berberis Prunus

INDICATIONS AND USAGE

Under age 2: Consult a doctor.

DOSAGE AND ADMINISTRATION

Directions: Apply to skin in and around nose as needed.

ACTIVE INGREDIENT

Active Ingredients: 100 gm contains: 50 gm Prunus spinosa (Blackthorn) 1X; Berberis (Barberry) 1X, Citrus (Lemon) 2X, Cydonia (Quince) 2X

INACTIVE INGREDIENT

Inactive Ingredients: Lanolin, Organic olive oil, Sunflower seed oil, Beeswax, Cajeput oil, Colloidal silica, Eucalyptus oil, Organic cane alcohol, Citric acid, Sorbic acid, Tea tree oil, Peruvian balsam, Grapefruit seed extract

Prepared using rhythmical processes.

PURPOSE

Use: Temporary relief of nasal congestion.

KEEP OUT OF REACH OF CHILDREN.

KEEP OUT OF REACH OF CHILDREN
Warnings: Claims based on traditional homeopathic practice, not accepted medical evidence. Not FDA evaluated. Do not use if allergic to any ingredient. Consult a doctor before use for serious conditions, if conditions worsen or persist, or accidental ingestion occurs. If pregnant or nursing, consult a doctor before use. Avoid contact with eyes. Do not use if safety seal on bag is broken or missing.

Questions? Call 866.642.2858
Made with care by Uriel, East Troy, WI 53120
shopuriel.com Lot: